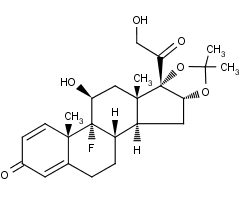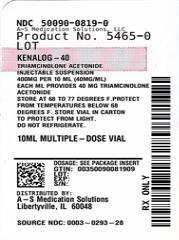 DRUG LABEL: KENALOG-40
NDC: 50090-0819 | Form: INJECTION, SUSPENSION
Manufacturer: A-S Medication Solutions
Category: prescription | Type: HUMAN PRESCRIPTION DRUG LABEL
Date: 20260105

ACTIVE INGREDIENTS: TRIAMCINOLONE ACETONIDE 40 mg/1 mL
INACTIVE INGREDIENTS: sodium chloride; benzyl alcohol; polysorbate 80; sodium hydroxide; hydrochloric acid; nitrogen; CELLULOSE GUM

KENALOG-40

NOT FOR USE IN NEONATES
CONTAINS BENZYL ALCOHOL

For Intramuscular or Intra-articular Use Only
NOT FOR INTRAVENOUS, INTRADERMAL, INTRAOCULAR, EPIDURAL, OR INTRATHECAL USE

DESCRIPTION

KENALOG®-40 Injection and KENALOG®-80 Injection (triamcinolone acetonide injectable suspension, USP) are a synthetic glucocorticoid corticosteroid with anti-inflammatory action. THESE FORMULATION ARE SUITABLE FOR INTRAMUSCULAR AND INTRA-ARTICULAR USE ONLY. THESE FORMULATION ARE NOT FOR INTRADERMAL INJECTION.

KENALOG®-40 Injection: Each mL of the sterile aqueous suspension provides 40 mg triamcinolone acetonide, with 0.66% sodium chloride for isotonicity, 0.99% (w/v) benzyl alcohol as a preservative, 0.63% carboxymethylcellulose sodium, and 0.04% polysorbate 80. Sodium hydroxide or hydrochloric acid may be present to adjust pH to 5.0 to 7.5. At the time of manufacture, the air in the container is replaced by nitrogen.

KENALOG®-80 Injection: Each mL of the sterile aqueous suspension provides 80 mg triamcinolone acetonide, with 0.66% sodium chloride for isotonicity, 0.99% (w/v) benzyl alcohol as a preservative, 0.63% carboxymethylcellulose sodium, and 0.04% polysorbate 80. Sodium hydroxide or hydrochloric acid may be present to adjust pH to 5.0 to 7.5. At the time of manufacture, the air in the container is replaced by nitrogen.

The chemical name for triamcinolone acetonide is 9-Fluoro-11β,16α,17,21-tetrahydroxypregna-1,4-diene-3,20-dione cyclic 16,17-acetal with acetone. Its structural formula is:

MW 434.50

Triamcinolone acetonide occurs as a white to cream-colored, crystalline powder having not more than a slight odor and is

practically insoluble in water and very soluble in alcohol.

CLINICAL PHARMACOLOGY

Glucocorticoids, naturally occurring and synthetic, are adrenocortical steroids that are readily absorbed from the gastrointestinal tract.

Naturally occurring glucocorticoids (hydrocortisone and cortisone), which also have salt-retaining properties, are used as replacement therapy in adrenocortical deficiency states. Synthetic analogs such as triamcinolone are primarily used for their anti-inflammatory effects in disorders of many organ systems.

KENALOG-40 Injection and KENALOG-80 Injection have an extended duration of effect which may be sustained over a period of several weeks. Studies indicate that following a single intramuscular dose of 60 mg to 100 mg of triamcinolone acetonide, adrenal suppression occurs within 24 to 48 hours and then gradually returns to normal, usually in 30 to 40 days. This finding correlates closely with the extended duration of therapeutic action achieved with the drug.

INDICATIONS AND USAGE

Intramuscular

Where oral therapy is not feasible, injectable corticosteroid therapy, including KENALOG-40 Injection and KENALOG-80 Injection (triamcinolone acetonide injectable suspension, USP) is indicated for intramuscular use as follows:

Allergic states: Control of severe or incapacitating allergic conditions intractable to adequate trials of conventional treatment in asthma, atopic dermatitis, contact dermatitis, drug hypersensitivity reactions, perennial or seasonal allergic rhinitis, serum sickness, transfusion reactions.

Dermatologic diseases: Bullous dermatitis herpetiformis, exfoliative erythroderma, mycosis fungoides, pemphigus, severe erythema multiforme (Stevens-Johnson syndrome).

Endocrine disorders: Primary or secondary adrenocortical insufficiency (hydrocortisone or cortisone is the drug of choice; synthetic analogs may be used in conjunction with mineralocorticoids where applicable; in infancy, mineralocorticoid supplementation is of particular importance), congenital adrenal hyperplasia, hypercalcemia associated with cancer, nonsuppurative thyroiditis.

Gastrointestinal diseases: To tide the patient over a critical period of the disease in regional enteritis and ulcerative colitis.

Hematologic disorders: Acquired (autoimmune) hemolytic anemia, Diamond-Blackfan anemia, pure red cell aplasia, selected cases of secondary thrombocytopenia.

Miscellaneous: Trichinosis with neurologic or myocardial involvement, tuberculous meningitis with subarachnoid block or impending block when used with appropriate antituberculous chemotherapy.

Neoplastic diseases: For the palliative management of leukemias and lymphomas.

Nervous system: Acute exacerbations of multiple sclerosis; cerebral edema associated with primary or metastatic brain tumor or craniotomy.

Ophthalmic diseases: Sympathetic ophthalmia, temporal arteritis, uveitis, and ocular inflammatory conditions unresponsive to topical corticosteroids.

Renal diseases: To induce diuresis or remission of proteinuria in idiopathic nephrotic syndrome or that due to lupus erythematosus.

Respiratory diseases: Berylliosis, fulminating or disseminated pulmonary tuberculosis when used concurrently with appropriate antituberculous chemotherapy, idiopathic eosinophilic pneumonias, symptomatic sarcoidosis.

Rheumatic disorders: As adjunctive therapy for short-term administration (to tide the patient over an acute episode or exacerbation) in acute gouty arthritis; acute rheumatic carditis; ankylosing spondylitis; psoriatic arthritis; rheumatoid arthritis, including juvenile rheumatoid arthritis (selected cases may require low-dose maintenance therapy). For the treatment of dermatomyositis, polymyositis, and systemic lupus erythematosus.

Intra-Articular

The intra-articular or soft tissue administration of KENALOG-40 Injection and KENALOG-80 Injection are indicated as adjunctive therapy for short-term administration (to tide the patient over an acute episode or exacerbation) in acute gouty arthritis, acute and subacute bursitis, acute nonspecific tenosynovitis, epicondylitis, rheumatoid arthritis, synovitis of osteoarthritis.

CONTRAINDICATIONS

KENALOG-40 Injection and KENALOG-80 Injection are contraindicated in patients who are hypersensitive to any components of this product (see WARNINGS: General).

Intramuscular corticosteroid preparations are contraindicated for idiopathic thrombocytopenic purpura.

WARNINGS

Serious Neurologic Adverse Reactions with Epidural Administration

Serious neurologic events, some resulting in death, have been reported with epidural injection of corticosteroids (see WARNINGS: Neurologic). Specific events reported include, but are not limited to, spinal cord infarction, paraplegia, quadriplegia, cortical blindness, and stroke. These serious neurologic events have been reported with and without use of fluoroscopy. The safety and effectiveness of epidural administration of corticosteroids have not been established, and corticosteroids are not approved for this use.

General

Exposure to excessive amounts of benzyl alcohol has been associated with toxicity (hypotension, metabolic acidosis), particularly in neonates, and an increased incidence of kernicterus, particularly in small preterm infants. There have been rare reports of deaths, primarily in preterm infants, associated with exposure to excessive amounts of benzyl alcohol. The amount of benzyl alcohol from medications is usually considered negligible compared to that received in flush solutions containing benzyl alcohol. Administration of high dosages of medications containing this preservative must take into account the total amount of benzyl alcohol administered. The amount of benzyl alcohol at which toxicity may occur is not known. If the patient requires more than the recommended dosages or other medications containing this preservative, the practitioner must consider the daily metabolic load of benzyl alcohol from these combined sources (see PRECAUTIONS: Pediatric Use).

Rare instances of anaphylaxis have occurred in patients receiving corticosteroid therapy (see ADVERSE REACTIONS). Cases of serious anaphylaxis, including death, have been reported in individuals receiving triamcinolone acetonide injection, regardless of the route of administration.

Because KENALOG-40 Injection and KENALOG-80 Injection (triamcinolone acetonide injectable suspension, USP) are suspensions, they should not be administered intravenously.

Unless a deep intramuscular injection is given, local atrophy is likely to occur. (For recommendations on injection techniques, see DOSAGE AND ADMINISTRATION.) Due to the significantly higher incidence of local atrophy when the material is injected into the deltoid area, this injection site should be avoided in favor of the gluteal area.

Increased dosage of rapidly acting corticosteroids is indicated in patients on corticosteroid therapy subjected to any unusual stress before, during, and after the stressful situation. KENALOG-40 Injection and KENALOG-80 Injection are long-acting preparations, and are not suitable for use in acute stress situations. To avoid drug-induced adrenal insufficiency, supportive dosage may be required in times of stress (such as trauma, surgery, or severe illness) both during treatment with KENALOG-40 Injection and KENALOG-80 Injection and for a year afterwards.

Results from one multicenter, randomized, placebo-controlled study with methylprednisolone hemisuccinate, an intravenous corticosteroid, showed an increase in early (at 2 weeks) and late (at 6 months) mortality in patients with cranial trauma who were determined not to have other clear indications for corticosteroid treatment. High doses of systemic corticosteroids, including KENALOG-40 Injection and KENALOG-80 Injection, should not be used for the treatment of traumatic brain injury.

Cardio-Renal

Average and large doses of corticosteroids can cause elevation of blood pressure, salt and water retention, and increased excretion of potassium. These effects are less likely to occur with the synthetic derivatives except when they are used in large doses. Dietary salt restriction and potassium supplementation may be necessary (see PRECAUTIONS). All corticosteroids increase calcium excretion.

Literature reports suggest an apparent association between use of corticosteroids and left ventricular free wall rupture after a recent myocardial infarction; therefore, therapy with corticosteroids should be used with great caution in these patients.

There have been cases reported in which concomitant use of amphotericin B and hydrocortisone was followed by cardiac enlargement and congestive heart failure (see PRECAUTIONS: Drug Interactions: Amphotericin B injection and potassium- depleting agents).

Endocrine

Corticosteroids can produce reversible hypothalamic-pituitary-adrenal (HPA) axis suppression with the potential for glucocorticosteroid insufficiency after withdrawal of treatment.

Metabolic clearance of corticosteroids is decreased in hypothyroid patients and increased in hyperthyroid patients. Changes in thyroid status of the patient may necessitate adjustment in dosage.

Immunosuppression and Increased Risk of Infection

Corticosteroids, including KENALOG-40 and KENALOG-80, suppress the immune system and increase the risk of infection with any pathogen, including viral, bacterial, fungal, protozoan, or helminthic pathogens. Corticosteroids can:
• Reduce resistance to new infections
• Exacerbate existing infections
• Increase the risk of disseminated infections
• Increase the risk of reactivation or exacerbation of latent infections
• Mask some signs of infection

Corticosteroid-associated infections can be mild but can be severe and at times fatal. The rate of infectious complications increases with increasing corticosteroid dosages.

Monitor for the development of infection and consider KENALOG-40 or KENALOG-80 withdrawal or dosage reduction as needed.

Do not administer KENALOG-40 and KENALOG-80 by an intraarticular, intrabursal, or intratendinous route in the presence of acute local infection.

Tuberculosis

If KENALOG-40 or KENALOG-80 is used to treat a condition in patients with latent tuberculosis or tuberculin reactivity, reactivation of the disease may occur. Closely monitor such patients for reactivation. During prolonged KENALOG-40 or KENALOG-80 therapy, patients with latent tuberculosis or tuberculin reactivity should receive chemoprophylaxis.

Varicella Zoster and Measles Viral Infections

Varicella and measles can have a serious or even fatal course in non-immune patients receiving corticosteroids, including KENALOG-40 or KENALOG-80. In corticosteroid-treated patients who have not had these diseases or are non-immune, particular care should be taken to avoid exposure to varicella and measles:
• If a KENALOG-40- or KENALOG-80- treated patient is exposed to varicella, prophylaxis with varicella zoster immune globulin (VZIG) may be indicated. If varicella develops, treatment with antiviral agents may be considered.
• If a KENALOG-40- or KENALOG-80-treated patient is exposed to measles, prophylaxis with immunoglobulin (IG) may be indicated.

Hepatitis B virus reactivation can occur in patients who are hepatitis B carriers treated with immunosuppressive dosages of corticosteroids, including KENALOG-40 and KENALOG-80. Reactivation can also occur infrequently in corticosteroid-treated patients who appear to have resolved hepatitis B infection.

Screen patients for hepatitis B infection before initiating immunosuppressive (e.g., prolonged) treatment with KENALOG-40 and KENALOG-80. For patients who show evidence of hepatitis B infection, recommend consultation with physicians with expertise in managing hepatitis B regarding monitoring and consideration for hepatitis B antiviral therapy.

Fungal Infections

Corticosteroids, including KENALOG-40 and KENALOG-80, may exacerbate systemic fungal infections; therefore, avoid KENALOG-40 and KENALOG-80 use in the presence of such infections unless KENALOG-40 or KENALOG-80 is needed to control drug reactions. For patients on chronic KENALOG-40 or KENALOG-80 therapy who develop systemic fungal infections, KENALOG-40 or KENALOG-80 withdrawal or dosage reduction is recommended.

Amebiasis

Corticosteroids, including KENALOG-40 and KENALOG-80, may activate latent amebiasis. Therefore, it is recommended that latent amebiasis or active amebiasis be ruled out before initiating KENALOG-40 or KENALOG-80 in patients who have spent time in the tropics or patients with unexplained diarrhea.

Strongyloides Infestation

Corticosteroids, including KENALOG-40 and KENALOG-80, should be used with great care in patients with known or suspected Strongyloides (threadworm) infestation. In such patients, corticosteroid-induced immunosuppression may lead to Strongyloides hyperinfection and dissemination with widespread larval migration, often accompanied by severe enterocolitis and potentially fatal gram-negative septicemia.

Cerebral Malaria

Avoid corticosteroids, including KENALOG-40 and KENALOG-80, in patients with cerebral malaria.

Vaccination

Administration of live or live, attenuated vaccines is contraindicated in patients receiving immunosuppressive doses of corticosteroids. Killed or inactivated vaccines may be administered. However, the response to such vaccines cannot be predicted. Immunization procedures may be undertaken in patients who are receiving corticosteroids as replacement therapy, e.g., for Addison’s disease.

Neurologic

Epidural and intrathecal administration of this product is not recommended. Reports of serious medical events, including death, have been associated with epidural and intrathecal routes of corticosteroid administration (see ADVERSE REACTIONS: Gastrointestinal and Neurologic/Psychiatric).

Ophthalmic

Use of corticosteroids may produce posterior subcapsular cataracts, glaucoma with possible damage to the optic nerves, and may enhance the establishment of secondary ocular infections due to bacteria, fungi, or viruses. The use of oral corticosteroids is not recommended in the treatment of optic neuritis and may lead to an increase in the risk of new episodes. Corticosteroids should not be used in active ocular herpes simplex.

Adequate studies to demonstrate the safety of KENALOG-40 Injection and KENALOG-80 Injection use by intraturbinal, subconjunctival, sub-Tenons, retrobulbar, and intraocular (intravitreal) injections have not been performed. Endophthalmitis, eye inflammation, increased intraocular pressure, and visual disturbances including vision loss have been reported with intravitreal administration. Administration of KENALOG-40 Injection and KENALOG-80 Injection intraocularly or into the nasal turbinates is not recommended.

Intraocular injection of corticosteroid formulations containing benzyl alcohol, such as KENALOG-40 Injection, is not recommended because of potential toxicity from the benzyl alcohol.

Kaposi’s sarcoma has been reported to occur in patients receiving corticosteroid therapy, most often for chronic conditions. Discontinuation of corticosteroids may result in clinical improvement of Kaposi’s sarcoma.

PRECAUTIONS

General

This product, like many other steroid formulations, is sensitive to heat. Therefore, it should not be autoclaved when it is desirable to sterilize the exterior of the vial.

The lowest possible dose of corticosteroid should be used to control the condition under treatment. When reduction in dosage is possible, the reduction should be gradual.

Since complications of treatment with glucocorticoids are dependent on the size of the dose and the duration of treatment, a risk/benefit decision must be made in each individual case as to dose and duration of treatment and as to whether daily or intermittent therapy should be used.

Cardio-Renal

As sodium retention with resultant edema and potassium loss may occur in patients receiving corticosteroids, these agents should be used with caution in patients with congestive heart failure, hypertension, or renal insufficiency.

Endocrine

Drug-induced secondary adrenocortical insufficiency may be minimized by gradual reduction of dosage. This type of relative insufficiency may persist for months after discontinuation of therapy; therefore, in any situation of stress occurring during that period, hormone therapy should be reinstituted. Since mineralocorticoid secretion may be impaired, salt and/or a mineralocorticoid should be administered concurrently.

Gastrointestinal

Steroids should be used with caution in active or latent peptic ulcers, diverticulitis, fresh intestinal anastomoses, and nonspecific ulcerative colitis, since they may increase the risk of a perforation.

Signs of peritoneal irritation following gastrointestinal perforation in patients receiving corticosteroids may be minimal or absent.

There is an enhanced effect of corticosteroids in patients with cirrhosis.

Intra-Articular and Soft Tissue Administration

Intra-articularly injected corticosteroids may be systemically absorbed.

Appropriate examination of any joint fluid present is necessary to exclude a septic process.

A marked increase in pain accompanied by local swelling, further restriction of joint motion, fever, and malaise are suggestive of septic arthritis. If this complication occurs and the diagnosis of sepsis is confirmed, appropriate antimicrobial therapy should be instituted.

Injection of a steroid into an infected site is to be avoided. Local injection of a steroid into a previously infected joint is not usually recommended.

Corticosteroid injection into unstable joints is generally not recommended.

Intra-articular injection may result in damage to joint tissues (see ADVERSE REACTIONS: Musculoskeletal).

Musculoskeletal

Corticosteroids decrease bone formation and increase bone resorption both through their effect on calcium regulation (i.e., decreasing absorption and increasing excretion) and inhibition of osteoblast function. This, together with a decrease in the protein matrix of the bone secondary to an increase in protein catabolism, and reduced sex hormone production, may lead to inhibition of bone growth in pediatric patients and the development of osteoporosis at any age. Special consideration should be given to patients at increased risk of osteoporosis (i.e., postmenopausal women) before initiating corticosteroid therapy.

Neuro-Psychiatric

Although controlled clinical trials have shown corticosteroids to be effective in speeding the resolution of acute exacerbations of multiple sclerosis, they do not show that they affect the ultimate outcome or natural history of the disease. The studies do show that relatively high doses of corticosteroids are necessary to demonstrate a significant effect. (See DOSAGE AND ADMINISTRATION).

An acute myopathy has been observed with the use of high doses of corticosteroids, most often occurring in patients with disorders of neuromuscular transmission (e.g., myasthenia gravis), or in patients receiving concomitant therapy with neuromuscular blocking drugs (e.g., pancuronium). This acute myopathy is generalized, may involve ocular and respiratory muscles, and may result in quadriparesis. Elevation of creatinine kinase may occur. Clinical improvement or recovery after stopping corticosteroids may require weeks to years.

Psychiatric derangements may appear when corticosteroids are used, ranging from euphoria, insomnia, mood swings, personality changes, and severe depression to frank psychotic manifestations. Also, existing emotional instability or psychotic tendencies may be aggravated by corticosteroids.

Ophthalmic

Intraocular pressure may become elevated in some individuals. If steroid therapy is continued for more than 6 weeks, intraocular pressure should be monitored.

Information for Patients

Patients should be warned not to discontinue the use of corticosteroids abruptly or without medical supervision, to advise any medical attendants that they are taking corticosteroids, and to seek medical advice at once should they develop fever or other signs of infection.

Persons who are on corticosteroids should be warned to avoid exposure to chicken pox or measles. Patients should also be advised that if they are exposed, medical advice should be sought without delay.

Drug Interactions

Aminoglutethimide: Aminoglutethimide may lead to a loss of corticosteroid-induced adrenal suppression.

Amphotericin B injection and potassium-depleting agents: When corticosteroids are administered concomitantly with potassium-depleting agents (i.e., amphotericin B, diuretics), patients should be observed closely for development of hypokalemia. There have been cases reported in which concomitant use of amphotericin B and hydrocortisone was followed by cardiac enlargement and congestive heart failure.

Antibiotics: Macrolide antibiotics have been reported to cause a significant decrease in corticosteroid clearance.

Anticholinesterases: Concomitant use of anticholinesterase agents and corticosteroids may produce severe weakness in patients with myasthenia gravis. If possible, anticholinesterase agents should be withdrawn at least 24 hours before initiating corticosteroid therapy.

Anticoagulants, oral: Coadministration of corticosteroids and warfarin usually results in inhibition of response to warfarin, although there have been some conflicting reports. Therefore, coagulation indices should be monitored frequently to maintain the desired anticoagulant effect.

Antidiabetics: Because corticosteroids may increase blood glucose concentrations, dosage adjustments of antidiabetic agents may be required.

Antitubercular drugs: Serum concentrations of isoniazid may be decreased.

Cholestyramine: Cholestyramine may increase the clearance of corticosteroids.

Cyclosporine: Increased activity of both cyclosporine and corticosteroids may occur when the two are used concurrently. Convulsions have been reported with this concurrent use.

CYP3A4 inhibitors: Triamcinolone acetonide is a substrate of CYP3A4. Ketoconazole has been reported to decrease the metabolism of certain corticosteroids by up to 60%, leading to an increased risk of corticosteroid side effects. Co-administration of other strong CYP3A4 inhibitors (e.g., ritonavir, atazanavir, clarithromycin, indinavir, itraconazole, nefazodone, nelfinavir, saquinavir, telithromycin, cobicistat-containing products) with KENALOG-40 Injection may cause increased plasma concentration of triamcinolone leading to adverse reactions. (See ADVERSE REACTIONS.) During postmarketing use, there have been reports of clinically significant drug interactions in patients receiving triamcinolone acetonide and strong CYP3A4 inhibitors (e.g., ritonavir). (See WARNINGS, Endocrine and PRECAUTIONS, Endocrine.) Consider the benefit-risk of concomitant use and monitor for systemic corticosteroid side effects.

Digitalis glycosides: Patients on digitalis glycosides may be at increased risk of arrhythmias due to hypokalemia.

Estrogens, including oral contraceptives: Estrogens may decrease the hepatic metabolism of certain corticosteroids, thereby increasing their effect.

Hepatic enzyme inducers (e.g., barbiturates, phenytoin, carbamazepine, rifampin): Drugs which induce hepatic microsomal drug metabolizing enzyme activity may enhance the metabolism of corticosteroids and require that the dosage of the corticosteroid be increased.

Nonsteroidal anti-inflammatory drugs (NSAIDs): Concomitant use of aspirin (or other nonsteroidal anti-inflammatory drugs) and corticosteroids increases the risk of gastrointestinal side effects. Aspirin should be used cautiously in conjunction with corticosteroids in hypoprothrombinemia. The clearance of salicylates may be increased with concurrent use of corticosteroids.

Skin tests: Corticosteroids may suppress reactions to skin tests.

Vaccines: Patients on prolonged corticosteroid therapy may exhibit a diminished response to toxoids and live or inactivated vaccines due to inhibition of antibody response. Corticosteroids may also potentiate the replication of some organisms contained in live attenuated vaccines. Routine administration of vaccines or toxoids should be deferred until corticosteroid therapy is discontinued if possible (see WARNINGS: Immunosuppression and Increased Risk of Infection, Vaccination).

Carcinogenesis, Mutagenesis, Impairment of Fertility

No adequate studies have been conducted in animals to determine whether corticosteroids have a potential for carcinogenesis or mutagenesis.

Steroids may increase or decrease motility and number of spermatozoa in some patients.

Teratogenic Effects

Corticosteroids have been shown to be teratogenic in many species when given in doses equivalent to the human dose. Animal studies in which corticosteroids have been given to pregnant mice, rats, and rabbits have yielded an increased incidence of cleft palate in the offspring. There are no adequate and well-controlled studies in pregnant women. Corticosteroids should be used during pregnancy only if the potential benefit justifies the potential risk to the fetus. Infants born to mothers who have received corticosteroids during pregnancy should be carefully observed for signs of hypoadrenalism.

Nursing Mothers

Systemically administered corticosteroids appear in human milk and could suppress growth, interfere with endogenous corticosteroid production, or cause other untoward effects. Caution should be exercised when corticosteroids are administered to a nursing woman.

Pediatric Use

This product contains benzyl alcohol as a preservative. Benzyl alcohol, a component of this product, has been associated with serious adverse events and death, particularly in pediatric patients. The “gasping syndrome” (characterized by central nervous system depression, metabolic acidosis, gasping respirations, and high levels of benzyl alcohol and its metabolites found in the blood and urine) has been associated with benzyl alcohol dosages >99 mg/kg/day in neonates and low-birth-weight neonates. Additional symptoms may include gradual neurological deterioration, seizures, intracranial hemorrhage, hematologic abnormalities, skin breakdown, hepatic and renal failure, hypotension, bradycardia, and cardiovascular collapse. Although normal therapeutic doses of this product deliver amounts of benzyl alcohol that are substantially lower than those reported in association with the “gasping syndrome,” the minimum amount of benzyl alcohol at which toxicity may occur is not known. Premature and low-birth-weight infants, as well as patients receiving high dosages, may be more likely to develop toxicity. Practitioners administering this and other medications containing benzyl alcohol should consider the combined daily metabolic load of benzyl alcohol from all sources.

The efficacy and safety of corticosteroids in the pediatric population are based on the well-established course of effect of corticosteroids which is similar in pediatric and adult populations. Published studies provide evidence of efficacy and safety in pediatric patients for the treatment of nephrotic syndrome (>2 years of age), and aggressive lymphomas and leukemias (>1 month of age). Other indications for pediatric use of corticosteroids, e.g., severe asthma and wheezing, are based on adequate and well-controlled trials conducted in adults, on the premises that the course of the diseases and their pathophysiology are considered to be substantially similar in both populations.

The adverse effects of corticosteroids in pediatric patients are similar to those in adults (see ADVERSE REACTIONS). Like adults, pediatric patients should be carefully observed with frequent measurements of blood pressure, weight, height, intraocular pressure, and clinical evaluation for the presence of infection, psychosocial disturbances, thromboembolism, peptic ulcers, cataracts, and osteoporosis. Pediatric patients who are treated with corticosteroids by any route, including systemically administered corticosteroids, may experience a decrease in their growth velocity. This negative impact of corticosteroids on growth has been observed at low systemic doses and in the absence of laboratory evidence of HPA axis suppression (i.e., cosyntropin stimulation and basal cortisol plasma levels). Growth velocity may therefore be a more sensitive indicator of systemic corticosteroid exposure in pediatric patients than some commonly used tests of HPA axis function. The linear growth of pediatric patients treated with corticosteroids should be monitored, and the potential growth effects of prolonged treatment should be weighed against clinical benefits obtained and the availability of treatment alternatives. In order to minimize the potential growth effects of corticosteroids, pediatric patients should be titrated to the lowest effective dose.

Geriatric Use

No overall differences in safety or effectiveness were observed between elderly subjects and younger subjects, and other reported clinical experience has not identified differences in responses between the elderly and younger patients, but greater sensitivity of some older individuals cannot be ruled out.

ADVERSE REACTIONS

(listed alphabetically under each subsection)

The following adverse reactions may be associated with corticosteroid therapy:

Allergic reactions: Anaphylaxis including death, and angioedema.

Cardiovascular: Bradycardia, cardiac arrest, cardiac arrhythmias, cardiac enlargement, circulatory collapse, congestive heart failure, fat embolism, hypertension, hypertrophic cardiomyopathy in premature infants, myocardial rupture following recent myocardial infarction (see WARNINGS), pulmonary edema, syncope, tachycardia, thromboembolism, thrombophlebitis, vasculitis.

Dermatologic: Acne, allergic dermatitis, cutaneous and subcutaneous atrophy, dry scaly skin, ecchymoses and petechiae, edema, erythema, hyperpigmentation, hypopigmentation, impaired wound healing, increased sweating, lupus erythematosus-like lesions, purpura, rash, sterile abscess, striae, suppressed reactions to skin tests, thin fragile skin, thinning scalp hair, urticaria.

Endocrine: Decreased carbohydrate and glucose tolerance, development of cushingoid state, glycosuria, hirsutism, hypertrichosis, increased requirements for insulin or oral hypoglycemic agents in diabetes, manifestations of latent diabetes mellitus, menstrual irregularities, postmenopausal vaginal hemorrhage, secondary adrenocortical and pituitary unresponsiveness (particularly in times of stress, as in trauma, surgery, or illness), suppression of growth in pediatric patients.

Fluid and electrolyte disturbances: Congestive heart failure in susceptible patients, fluid retention, hypokalemic alkalosis, potassium loss, sodium retention.

Gastrointestinal: Abdominal distention, bowel/bladder dysfunction (after intrathecal administration
[see WARNINGS: Neurologic]), elevation in serum liver enzyme levels (usually reversible upon discontinuation), hepatomegaly, increased appetite, nausea, pancreatitis, peptic ulcer with possible perforation and hemorrhage, perforation of the small and large intestine (particularly in patients with inflammatory bowel disease), ulcerative esophagitis.

Metabolic: Negative nitrogen balance due to protein catabolism.

Musculoskeletal: Aseptic necrosis of femoral and humeral heads, calcinosis (following intra-articular or intralesional use), Charcot-like arthropathy, loss of muscle mass, muscle weakness, osteoporosis, pathologic fracture of long bones, post injection flare (following intra-articular use), steroid myopathy, tendon rupture, vertebral compression fractures.

Neurologic/Psychiatric: Convulsions, depression, emotional instability, euphoria, headache, increased intracranial pressure with papilledema (pseudotumor cerebri) usually following discontinuation of treatment, insomnia, mood swings, neuritis, neuropathy, paresthesia, personality changes, psychiatric disorders, vertigo. Arachnoiditis, meningitis, paraparesis/paraplegia, and sensory disturbances have occurred after intrathecal administration. Spinal cord infarction, paraplegia, quadriplegia, cortical blindness, and stroke (including brainstem) have been reported after epidural administration of corticosteroids (see WARNINGS: Serious Neurologic Adverse Reactions with Epidural Administration and WARNINGS: Neurologic).

Ophthalmic: Exophthalmos, glaucoma, increased intraocular pressure, posterior subcapsular cataracts, rare instances of blindness associated with periocular injections.

Other: Abnormal fat deposits, decreased resistance to infection, hiccups, increased or decreased motility and number of spermatozoa, malaise, moon face, weight gain.

OVERDOSAGE

Treatment of acute overdosage is by supportive and symptomatic therapy. For chronic overdosage in the face of severe disease requiring continuous steroid therapy, the dosage of the corticosteroid may be reduced only temporarily, or alternate day treatment may be introduced.

DOSAGE AND ADMINISTRATION

General

NOTE: CONTAINS BENZYL ALCOHOL (see PRECAUTIONS).

The initial dose of KENALOG-40 Injection and KENALOG-80 Injection may vary from 2.5 mg to 100 mg per day depending on the specific disease entity being treated (see Dosage section below). However, in certain overwhelming, acute, life-threatening situations, administration in dosages exceeding the usual dosages may be justified and may be in multiples of the oral dosages.

IT SHOULD BE EMPHASIZED THAT DOSAGE REQUIREMENTS ARE VARIABLE AND MUST BE INDIVIDUALIZED ON THE BASIS OF THE DISEASE UNDER TREATMENT AND THE RESPONSE OF THE PATIENT. After a favorable response is noted, the proper maintenance dosage should be determined by decreasing the initial drug dosage in small decrements at appropriate time intervals until the lowest dosage which will maintain an adequate clinical response is reached. Situations which may make dosage adjustments necessary are changes in clinical status secondary to remissions or exacerbations in the disease process, the patient’s individual drug responsiveness, and the effect of patient exposure to stressful situations not directly related to the disease entity under treatment. In this latter situation it may be necessary to increase the dosage of the corticosteroid for a period of time consistent with the patient’s condition. If after long-term therapy the drug is to be stopped, it is recommended that it be withdrawn gradually rather than abruptly.

SYSTEMIC

The suggested initial dose is 60 mg, injected deeply into the gluteal muscle. Atrophy of subcutaneous fat may occur if the injection is not properly given. Dosage is usually adjusted within the range of 40 mg to 80 mg, depending upon patient response and duration of relief. However, some patients may be well controlled on doses as low as 20 mg or less.

Hay fever or pollen asthma: Patients with hay fever or pollen asthma who are not responding to pollen administration and other conventional therapy may obtain a remission of symptoms lasting throughout the pollen season after a single injection of 40 mg to 100 mg.

In the treatment of acute exacerbations of multiple sclerosis, daily doses of 160 mg of triamcinolone for a week followed by 64 mg every other day for one month are recommended (see PRECAUTIONS: Neuro-Psychiatric).

In pediatric patients, the initial dose of triamcinolone may vary depending on the specific disease entity being treated. The range of initial doses is 0.11 mg/kg/day to 1.6 mg/kg/day in 3 or 4 divided doses (3.2 mg/m^2bsa/day to 48 mg/m^2bsa/day).

For the purpose of comparison, the following is the equivalent milligram dosage of the various glucocorticoids:

Cortisone, 25 | Triamcinolone, 4
Hydrocortisone, 20 | Paramethasone, 2
Prednisolone, 5 | Betamethasone, 0.75
Prednisone, 5 | Dexamethasone, 0.75
Methylprednisolone, 4

These dose relationships apply only to oral or intravenous administration of these compounds. When these substances or their derivatives are injected intramuscularly or into joint spaces, their relative properties may be greatly altered.

LOCAL

Intra-articular administration: A single local injection of triamcinolone acetonide is frequently sufficient, but several injections may be needed for adequate relief of symptoms.

Initial dose: 2.5 mg to 5 mg for smaller joints and from 5 mg to 15 mg for larger joints, depending on the specific disease entity being treated. For adults, doses up to 10 mg for smaller areas and up to 40 mg for larger areas have usually been sufficient. Single injections into several joints, up to a total of 80 mg, have been given.

GENERAL

STRICT ASEPTIC TECHNIQUE IS MANDATORY. The vial should be shaken before use to ensure a uniform suspension. Prior to withdrawal, the suspension should be inspected for clumping or granular appearance (agglomeration). Agglomeration occurs when the drug substance separates from the solution and appears as a white precipitate in the vial. An agglomerated product should be discarded and should not be used. After withdrawal, KENALOG-40 Injection and KENALOG-80 Injection should be injected without delay to prevent settling in the syringe. Careful technique should be employed to avoid the possibility of entering a blood vessel or introducing infection.

SYSTEMIC

For systemic therapy, injection should be made deeply into the gluteal muscle (see WARNINGS). For adults, a minimum needle length of 1½ inches is recommended. In obese patients, a longer needle may be required. Use alternative sites for subsequent injections.

LOCAL

For treatment of joints, the usual intra-articular injection technique should be followed. If an excessive amount of synovial fluid is present in the joint, some, but not all, should be aspirated to aid in the relief of pain and to prevent undue dilution of the steroid.

With intra-articular administration, prior use of a local anesthetic may often be desirable. Care should be taken with this kind of injection, particularly in the deltoid region, to avoid injecting the suspension into the tissues surrounding the site, since this may lead to tissue atrophy.

In treating acute nonspecific tenosynovitis, care should be taken to ensure that the injection of the corticosteroid is made into the tendon sheath rather than the tendon substance. Epicondylitis may be treated by infiltrating the preparation into the area of greatest tenderness.

HOW SUPPLIED

Product: 50090-0819

NDC: 50090-0819-0 10 mL in a VIAL, MULTI-DOSE / 1 in a CARTON

Bristol-Myers Squibb Company
Princeton, NJ 08543 USA

Revised: Aug 2024